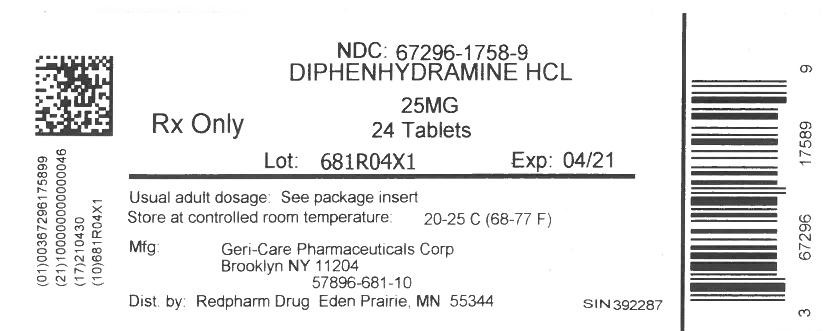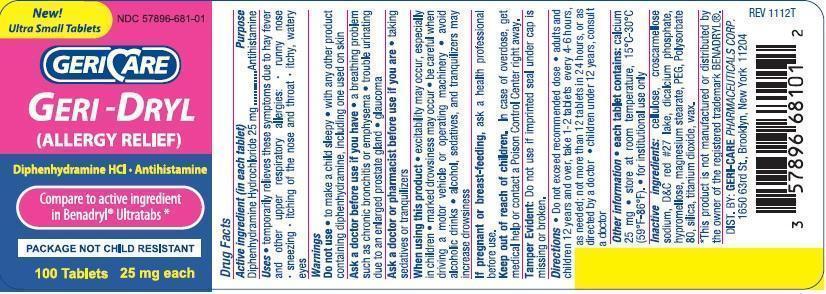 DRUG LABEL: Geri-Dryl allergy relief
NDC: 67296-1758 | Form: TABLET, COATED
Manufacturer: RedPharm Drug, Inc.
Category: otc | Type: HUMAN OTC DRUG LABEL
Date: 20200101

ACTIVE INGREDIENTS: DIPHENHYDRAMINE HYDROCHLORIDE 25 mg/1 1
INACTIVE INGREDIENTS: CARNAUBA WAX; SILICON DIOXIDE; CROSCARMELLOSE SODIUM; D&C RED NO. 27; HYPROMELLOSES; CELLULOSE, MICROCRYSTALLINE; CALCIUM PHOSPHATE, DIBASIC, DIHYDRATE; MAGNESIUM STEARATE; POLYETHYLENE GLYCOL 400; POLYSORBATE 80; TITANIUM DIOXIDE

Diphenhydramine 25mg

Active ingredient (in each tablet)

Diphenhydramine Hydrochloride 25mg

Purpose

Antihistamine

Uses

- temporarily relieves these symptoms due to hay fever and other upper respiratory allergies:
- runny nose

- sneezing

- itching of the nose and throat
- itchy, watery eyes

Warnings

Do not use

- to make a child sleepy
- with any other product containing diphenhydramine, including one used on skin

Ask a doctor before use if you have

- a breathing problem such as chronic bronchitis or emphysema
- trouble urinating due to an enlarged prostate gland
- glaucoma

Ask a doctor or pharmacist before use if you are

- taking sedatives or tranquilizers

When using this product

- excitability may occur, especially in children
- marked drowsiness may occur
- be careful when driving a motor vehicle or operating machinery
- avoid alcoholic drinks
- alcohol, sedatives and tranquilizers may increase drowsiness

If pregnant or breast-feeding, ask a health professional before use.

Keep out of reach of children. In case of overdose, get medical help or contact a Poison Control Center right away.

Directions

- do not exceed recommended dose
- adults and children 12 years and over, take 1 to 2 tablets every 4-6 hours, as needed; not more than 12 tablets in 24 hours, or as directed by a doctor
- children under 12 years: consult a doctor

Other information

- each tablet contains: calcium 25mg
- store at room temperature 15⁰C - 30⁰C (59⁰F - 86⁰F)
- for institutional use only

Inactive ingredients

cellulose, croscarmellose sodium, D&C red #27 lake, dicalcium phosphate, hypromellose, magnesium stearate, PEG, polysorbate 80, silica, titanium dioxide, wax.

package label

New! Ultra Small Tablets
NDC 57896-681-01

GERICARE
GERI-DRYL
(ALLERGY RELIEF)
Diphenhydramine HCl
Antihistamine
Compare to active ingredient in Benadryl Ultratabs
PACKAGE NOT CHILD RESISTANT
100 Tablets
25 mg each